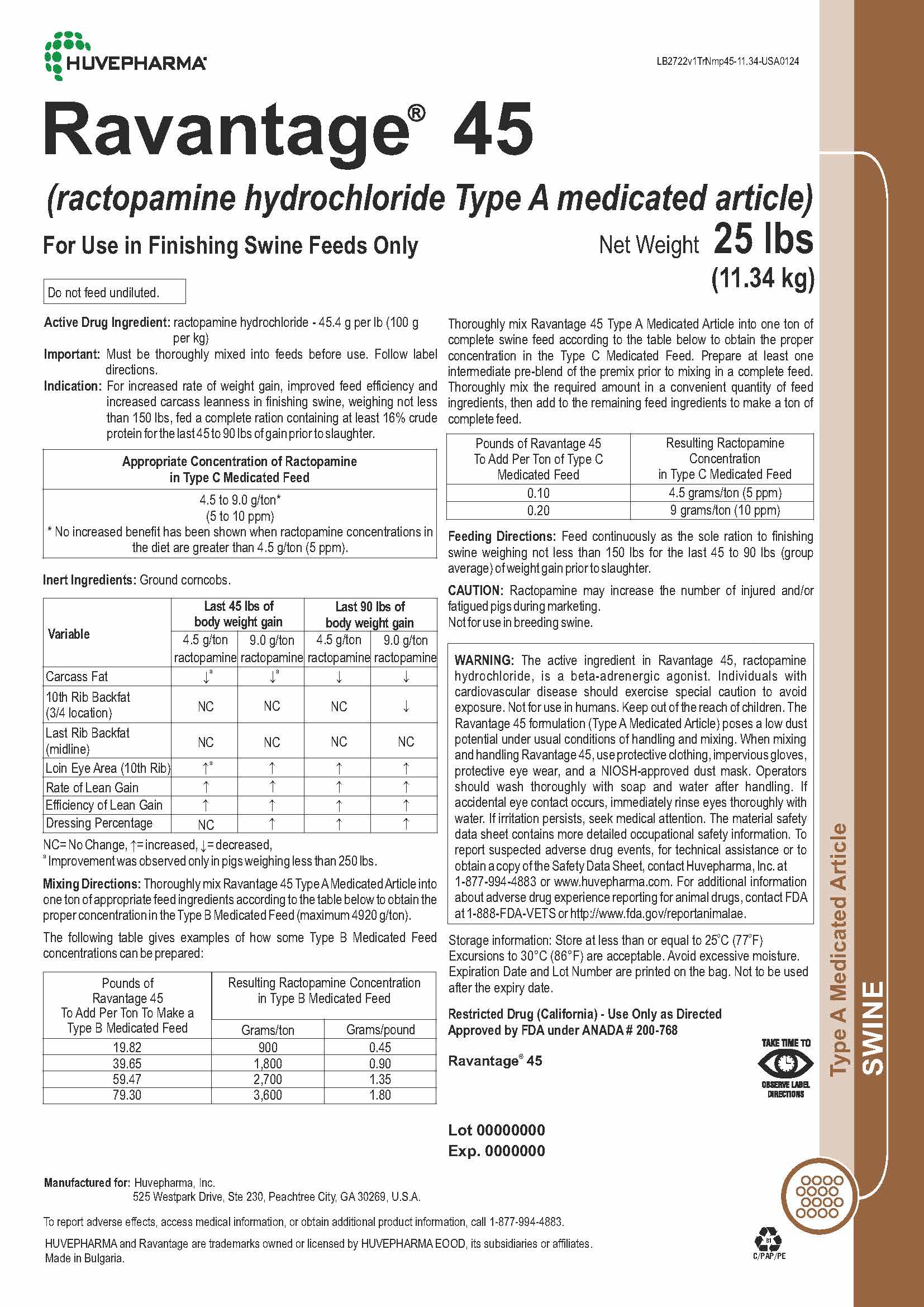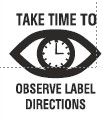 DRUG LABEL: Ravantage 45
NDC: 23243-5278 | Form: Powder
Manufacturer: Huvepharma, Inc
Category: animal | Type: OTC TYPE A MEDICATED ARTICLE ANIMAL DRUG LABEL
Date: 20250401

ACTIVE INGREDIENTS: ractopamine hydrochloride 45.4 g/0.45 kg
INACTIVE INGREDIENTS: povidone; CASTOR OIL; CORN COB

Ravantage® 45
(ractopamine hydrochloride Type A medicated article)

Huvepharma®

Ravantage® 45

(ractopamine hydrochloride Type A medicated article)

For Use in Finishing Swine Feeds Only

Net Weight 25 lbs

(11.34 kg)

Do not feed undiluted.

ACTIVE INGREDIENT

Active Drug Ingredient: ractopamine hydrochloride - 45.4 g per lb (100 g per kg)

Important: Must be thoroughly mixed into feeds before use. Follow label directions.

INDICATIONS AND USAGE

Indication: For increased rate of weight gain, improved feed efficiency and increased carcass leanness in finishing swine, weighing not less than 150 lbs, fed a complete ration containing at least 16% crude protein for the last 45 to 90 lbs of gain prior to slaughter.

Appropriate Concentration of Ractopamine in Type C
Medicated Feed

4.5 to 9.0 g/ton*
(5 to 10 ppm)
* No increased benefit has been shown when ractopamine concentrations in the diet are greater than 4.5 g/ton (5 ppm).

Inert Ingredients: Ground corncobs.

Variable | Last 45 lbs of body weight gain |  | Last 90 lbs of body weight gain
Variable | 4.5 g/ton ractopamine | 9.0 g/ton ractopamine | 4.5 g/ton ractopamine | 9.0 g/ton ractopamine
Carcass Fat | ↓a | ↓a | ↓ | ↓
10th Rib Backfat (3/4 location) | NC | NC | NC | ↓
Last Rib Backfat (midline) | NC | NC | NC | NC
Loin Eye Area (10th Rib) | ↑a | ↑ | ↑ | ↑
Rate of Lean Gain | ↑ | ↑ | ↑ | ↑
Efficiency of Lean Gain | ↑ | ↑ | ↑ | ↑
Dressing Percentage | NC | ↑ | ↑ | ↑
NC = No Change, ↑ = increased, ↓ = decreased,
a Improvement was observed only in pigs weighing less than 250 lbs.

Mixing Directions: Thoroughly mix Ravantage 45 Type A Medicated Article into one ton of appropriate feed ingredients according to the table below to obtain the proper concentration in the Type B Medicated Feed (maximum 4920 g/ton).

The following table gives examples of how some Type B Medicated Feed concentrations can be prepared:

Pounds of Ravantage 45 To Add Per Ton To Make a Type B Medicated Feed | Resulting Ractopamine Concentration in Type B Medicated Feed
Pounds of Ravantage 45 To Add Per Ton To Make a Type B Medicated Feed | Grams/ton | Grams/pound
19.82 | 900 | 0.45
39.65 | 1,800 | 0.90
59.47 | 2,700 | 1.35
79.30 | 3,600 | 1.80

Thoroughly mix Ravantage 45 Type A Medicated Article into one ton of complete swine feed according to the table below to obtain the proper concentration in the Type C Medicated Feed. Prepare at least one intermediate pre-blend of the premix prior to mixing in a complete feed. Thoroughly mix the required amount in a convenient quantity of feed ingredients, then add to the remaining feed ingredients to make a ton of complete feed.

Pounds of Ravantage 45 To Add Per Ton of Type C Medicated Feed | Resulting Ractopamine Concentration in Type C Medicated Feed
0.10 | 4.5 grams/ton (5 ppm)
0.20 | 9 grams/ton (10 ppm)

DOSAGE AND ADMINISTRATION

Feeding Directions: Feed continuously as the sole ration to finishing swine weighing not less than 150 lbs for the last 45 to 90 lbs (group average) of weight gain prior to slaughter.

CAUTION: Ractopamine may increase the number of injured and/or fatigued pigs during marketing.
Not for use in breeding swine.

BOXED WARNING

WARNING: The active ingredient in Ravantage 45, ractopamine hydrochloride, is a beta-adrenergic agonist. Individuals with cardiovascular disease should exercise special caution to avoid exposure. Not for use in humans. Keep out of the reach of children. The Ravantage 45 formulation (Type A Medicated Article) poses a low dust potential under usual conditions of handling and mixing. When mixing and handling Ravantage 45, use protective clothing, impervious gloves, protective eye wear, and a NIOSH-approved dust mask. Operators should wash thoroughly with soap and water after handling. If accidental eye contact occurs, immediately rinse eyes thoroughly with water. If irritation persists, seek medical attention. The material safety data sheet contains more detailed occupational safety information. To report suspected adverse drug events, for technical assistance or to obtain a copy of the Safety Data Sheet, contact Huvepharma, Inc. at 1-877-994-4883 or www.huvepharma.com. For additional information about adverse drug experience reporting for animal drugs, contact FDA at 1-888-FDA-VETS or http://www.fda.gov/reportanimalae.

STORAGE AND HANDLING

Storage information: Store at less than or equal to 25°C (77°F)
Excursions to 30°C (86°F) are acceptable. Avoid excessive moisture.
Expiration Date and Lot Number are printed on the bag.
Not to be used after the expiry date.

Restricted Drug (California) - Use Only as Directed
Approved by FDA under ANADA # 200-768

Ravantage® 45

Manufactured for: Huvepharma, Inc.
525 Westpark Drive, Ste 230, Peachtree City, GA 30269, U.S.A.

To report adverse effects, access medical information, or obtain additional product information, call 1-877-994-4883.

HUVEPHARMA and Ravantage are trademarks owned or licensed by HUVEPHARMA EOOD, its subsidiaries or affiliates.

Made in Bulgaria.